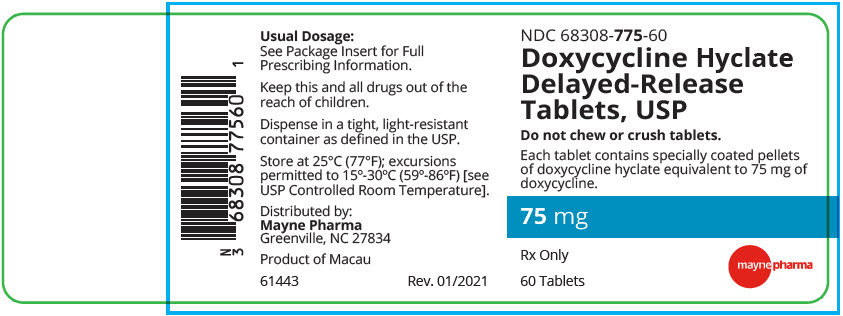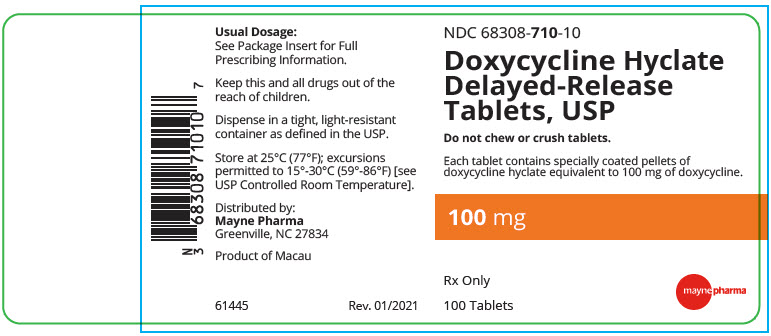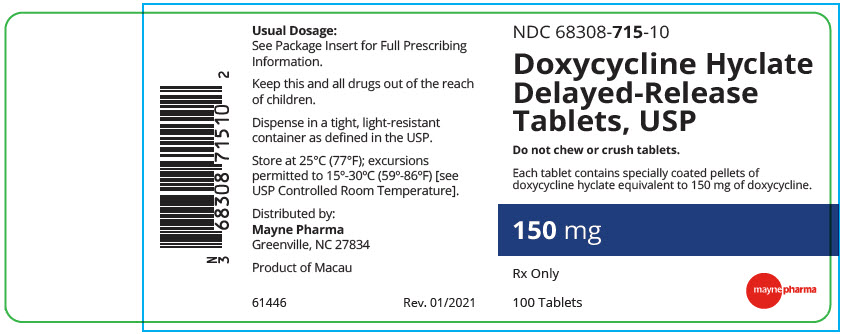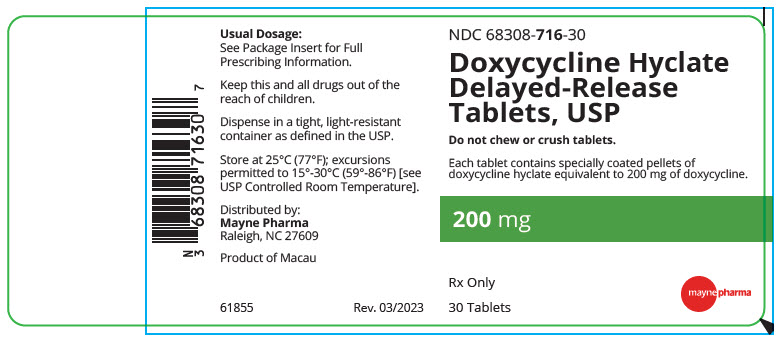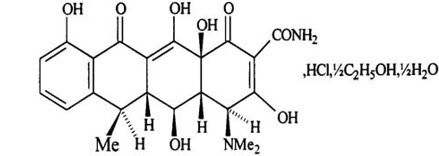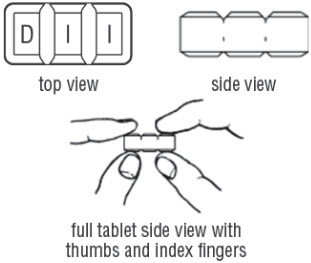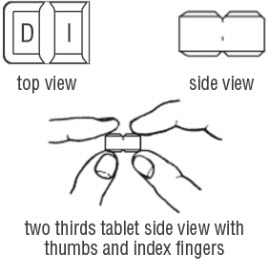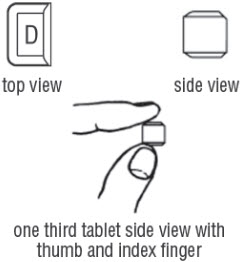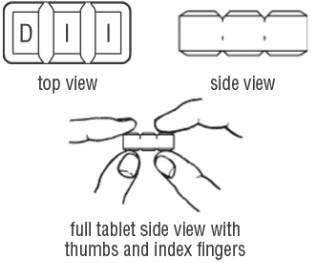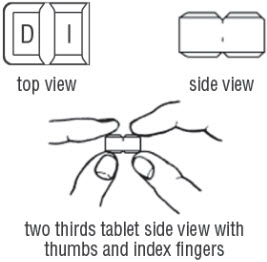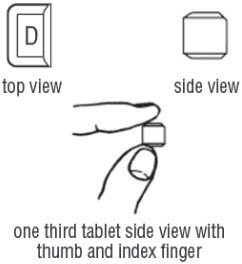 DRUG LABEL: Doxycycline Hyclate
NDC: 68308-775 | Form: TABLET, DELAYED RELEASE
Manufacturer: Mayne Pharma Commercial LLC
Category: prescription | Type: HUMAN PRESCRIPTION DRUG LABEL
Date: 20250414

ACTIVE INGREDIENTS: Doxycycline Hyclate 75 mg/1 1
INACTIVE INGREDIENTS: Lactose Monohydrate; Sodium Lauryl Sulfate; Sodium Chloride; Talc; Anhydrous Lactose; Starch, Corn; CROSPOVIDONE (120 .MU.M); Magnesium Stearate; Microcrystalline Cellulose; HYPROMELLOSE 2910 (6 MPA.S); HYPROMELLOSE PHTHALATE (24% PHTHALATE, 55 CST); TRIETHYL CITRATE

HIGHLIGHTS OF PRESCRIBING INFORMATION

These highlights do not include all the information needed to use DOXYCYCLINE HYCLATE DELAYED-RELEASE TABLETS safely and effectively. See full prescribing information for DOXYCYCLINE HYCLATE DELAYED-RELEASE TABLETS.
DOXYCYCLINE HYCLATE delayed-release tablets, for oral use.
Initial U.S. Approval: 1967

RECENT MAJOR CHANGES

Warnings and Precautions, Severe Skin Reactions (5.5) | 03/2025

1 INDICATIONS AND USAGE

Doxycycline hyclate delayed-release tablets are a tetracycline-class drug indicated for:

- Rickettsial infections (1.1)
- Sexually transmitted infections (1.2)
- Respiratory tract infections (1.3)
- Specific bacterial infections (1.4)
- Ophthalmic infections (1.5)
- Anthrax, including inhalational anthrax (post-exposure) (1.6)
- Alternative treatment for selected infections when penicillin is contraindicated (1.7)
- Adjunctive therapy in acute intestinal amebiasis and severe acne (1.8)
- Prophylaxis of malaria (1.9)

Usage

To reduce the development of drug-resistant bacteria and maintain the effectiveness of doxycycline hyclate delayed-release tablets and other antibacterial drugs, Doxycycline hyclate delayed-release tablets should be used only to treat or prevent infections that are proven or strongly suspected to be caused by bacteria. (1.10)

2 DOSAGE AND ADMINISTRATION

- Dosage in Adult Patients:
  - The usual dosage is 200 mg on the first day of treatment (administered 100 mg every 12 hours) followed by a maintenance dose of 100 mg daily. (2.1)
  - In the management of more severe infections (particularly chronic infections of the urinary tract), 100 mg every 12 hours is recommended. (2.1)
- Dosage in Pediatric Patients:
  - For all pediatric patients weighing less than 45 kg with severe or life-threatening infections (e.g., anthrax, Rocky Mountain spotted fever), the recommended dose is 2.2 mg per kg of body weight administered every 12 hours. Pediatric patients weighing 45 kg or more should receive the adult dose. (2.1)
  - For pediatric patients with less severe disease (greater than 8 years of age and weighing less than 45 kg), the recommended dose is 4.4 mg per kg of body weight divided into two doses on the first day of treatment, followed by a maintenance dose of 2.2 mg per kg of body weight (given as a single daily dose or divided into two doses). For pediatric patients weighing over 45 kg, the usual adult dose should be used. (2.1)

3 DOSAGE FORMS AND STRENGTHS

Doxycycline Hyclate Delayed-Release Tablets: 80 mg, and 200 mg (3)

4 CONTRAINDICATIONS

Doxycycline hyclate delayed-release tablets are contraindicated in persons who have shown hypersensitivity to any of the tetracyclines. (4)

5 WARNINGS AND PRECAUTIONS

- The use of drugs of the tetracycline-class during tooth development (last half of pregnancy, infancy and childhood to the age of 8 years) may cause permanent discoloration of the teeth (yellow-gray-brown). (5.1)
- Clostridioides difficile-associated diarrhea (CDAD) has been reported: Evaluate patients if diarrhea occurs. (5.2)
- Photosensitivity manifested by an exaggerated sunburn reaction has been observed in some individuals taking tetracyclines. Limit sun exposure. (5.3)
- Overgrowth of non-susceptible organisms, including fungi, may occur. If such infections occur, discontinue use and institute appropriate therapy. (5.4)

6 ADVERSE REACTIONS

- Adverse reactions observed in patients receiving tetracyclines include anorexia, nausea, vomiting, diarrhea, rash, photosensitivity, urticaria, and hemolytic anemia. (6)

To report SUSPECTED ADVERSE REACTIONS, contact Mayne Pharma at 1-844-825-8500 or FDA at 1-800-FDA-1088 or www.fda.gov/medwatch.

7 DRUG INTERACTIONS

- Patients who are on anticoagulant therapy may require downward adjustment of their anticoagulant dosage (7.1)
- Avoid co-administration of tetracyclines with penicillin (7.2)
- Absorption of tetracyclines, including Doxycycline hyclate delayed-release tablets, is impaired by antacids containing aluminum, calcium, or magnesium, bismuth subsalicylate and iron-containing preparations (7.3)
- Concurrent use of tetracyclines, including Doxycycline hyclate delayed-release tablets, may render oral contraceptives less effective (7.4)
- Barbiturates, carbamazepine and phenytoin decrease the half-life of doxycycline (7.5)

8 USE IN SPECIFIC POPULATIONS

- Tetracycline-class drugs can cause fetal harm when administered to a pregnant woman, but data for doxycycline are limited. (5.6, 8.1)
- Tetracyclines are excreted in human milk; however, the extent of absorption of doxycycline in the breastfed infant is not known. Doxycycline hyclate delayed-release tablets use during nursing should be avoided if possible. (8.2)

FULL PRESCRIBING INFORMATION

1 INDICATIONS AND USAGE

1.1 Rickettsial Infections

Doxycycline hyclate delayed-release tablets are indicated for treatment of Rocky Mountain spotted fever, typhus fever and the typhus group, Q fever, rickettsialpox, and tick fevers caused by Rickettsiae.

1.2 Sexually Transmitted Infections

Doxycycline hyclate delayed-release tablets are indicated for treatment of the following sexually transmitted infections:

- Uncomplicated urethral, endocervical or rectal infections caused by Chlamydia trachomatis.
- Nongonococcal urethritis caused by Ureaplasma urealyticum.
- Lymphogranuloma venereum caused by Chlamydia trachomatis.
- Granuloma inguinale caused by Klebsiella granulomatis.
- Uncomplicated gonorrhea caused by Neisseria gonorrhoeae.
- Chancroid caused by Haemophilus ducreyi.

1.3 Respiratory Tract Infections

Doxycycline hyclate delayed-release tablets are indicated for treatment of the following respiratory infections:

- Respiratory tract infections caused by Mycoplasma pneumoniae. Psittacosis (ornithosis) caused by Chlamydophila psittaci.
- Because many strains of the following groups of microorganisms have been shown to be resistant to doxycycline, culture and susceptibility testing are recommended.
- Doxycycline is indicated for treatment of infections caused by the following micro- organisms, when bacteriological testing indicates appropriate susceptibility to the drug:
  - Respiratory tract infections caused by Haemophilus influenzae.
  - Respiratory tract infections caused by Klebsiella species.
  - Upper respiratory infections caused by Streptococcus pneumoniae.

1.4 Specific Bacterial Infections

Doxycycline hyclate delayed-release tablets are indicated for treatment of the following specific bacterial infections:

- Relapsing fever due to Borrelia recurrentis.
- Plague due to Yersinia pestis.
- Tularemia due to Francisella tularensis.
- Cholera caused by Vibrio cholerae.
- Campylobacter fetus infections caused by Campylobacter fetus.
- Brucellosis due to Brucella species (in conjunction with streptomycin).
- Bartonellosis due to Bartonella bacilliformis.

Because many strains of the following groups of microorganisms have been shown to be resistant to doxycycline, culture and susceptibility testing are recommended.

Doxycycline hyclate delayed-release tablets are indicated for treatment of infections caused by the following gram- negative microorganisms, when bacteriological testing indicates appropriate susceptibility to the drug:

- Escherichia coli
- Enterobacter aerogenes
- Shigella species
- Acinetobacter species
- Urinary tract infections caused by Klebsiella species.

1.5 Ophthalmic Infections

Doxycycline hyclate delayed-release tablets are indicated for treatment of the following ophthalmic infections:

- Trachoma caused by Chlamydia trachomatis, although the infectious agent is not always eliminated as judged by immunofluorescence.
- Inclusion conjunctivitis caused by Chlamydia trachomatis.

1.6 Anthrax Including Inhalational Anthrax (Post-Exposure)

Doxycycline hyclate delayed-release tablets are indicated for the treatment of anthrax due to Bacillus anthracis, including inhalational anthrax (post-exposure): to reduce the incidence or progression of disease following exposure to aerosolized Bacillus anthracis.

1.7 Alternative Treatment for Selected Infections When Penicillin is Contraindicated

Doxycycline hyclate delayed-release tablets are indicated as an alternative treatment for the following selected infections when penicillin is contraindicated:

- Syphilis caused by Treponema pallidum.
- Yaws caused by Treponema pallidum subspecies pertenue.
- Vincent's infection caused by Fusobacterium fusiforme.
- Actinomycosis caused by Actinomyces israelii.
- Infections caused by Clostridium species.

1.8 Adjunctive Therapy for Acute Intestinal Amebiasis and Severe Acne

In acute intestinal amebiasis, doxycycline hyclate delayed-release tablets may be a useful adjunct to amebicides.

In severe acne, doxycycline may be useful adjunctive therapy.

1.9 Prophylaxis of Malaria

Doxycycline hyclate delayed-release tablets are indicated for the prophylaxis of malaria due to Plasmodium falciparum in short-term travelers (less than 4 months) to areas with chloroquine and/or pyrimethamine-sulfadoxine resistant strains [see Dosage and Administration (2.2) and Patient Counseling Information (17)].

1.10 Usage

To reduce the development of drug-resistant bacteria and maintain the effectiveness of doxycycline hyclate delayed-release tablets and other antibacterial drugs, doxycycline hyclate delayed-release tablets should be used only to treat or prevent infections that are proven or strongly suspected to be caused by susceptible bacteria. When culture and susceptibility information are available, they should be considered in selecting or modifying antibacterial therapy. In the absence of such data, local epidemiology and susceptibility patterns may contribute to the empiric selection of therapy.

2 DOSAGE AND ADMINISTRATION

2.1 Important Dosage and Administration Instructions

- Doxycycline hyclate delayed-release tablets are not substitutable on a mg per mg basis with other oral doxycyclines. To avoid prescribing errors, do not substitute doxycycline hyclate delayed-release tablets for other oral doxycyclines on a mg per mg basis because of differing bioavailability.
- Do not chew or crush tablets [see Dosage and Administration (2.4)].
- The recommended dosage, frequency of administration and weight-based dosage recommendations of doxycycline hyclate delayed-release tablets differ from that of the other tetracyclines [see Dosage and Administration (2.2, 2.3, 2.4)]. Exceeding the recommended dosage may result in
  an increased incidence of adverse reactions.
- Administer doxycycline hyclate delayed-release tablets with an adequate amount of fluid to wash down the drug and reduce the risk of esophageal irritation and ulceration [see Adverse Reactions (6.1)].
- If gastric irritation occurs, doxycycline hyclate delayed-release tablets may be given with food or milk [see Clinical Pharmacology (12.3)].

2.2 Switching from Doxycycline Hyclate Delayed-Release Tablets to Doxycycline Hyclate Delayed-Release Tablets (MPC)

When switching from doxycycline hyclate delayed-release tablets to doxycycline hyclate delayed-release tablets (MPC):

- A 60 mg dose of doxycycline hyclate delayed-release tablets (MPC) will replace a 50 mg dose of doxycycline hyclate delayed-release tablets
- A 120 mg dose of doxycycline hyclate delayed-release tablets (MPC) will replace a 100 mg dose of doxycycline hyclate delayed-release tablets

2.3 Dosage in Adult Patients

- The usual dosage of doxycycline hyclate delayed-release tablets is 200 mg on the first day of treatment (administered 100 mg every 12 hours), followed by a maintenance dose of 100 mg daily.
- The maintenance dose may be administered as a single dose or as 50 mg every 12 hours.
- In the management of more severe infections (particularly chronic infections of the urinary tract), 100 mg every 12 hours is recommended.
- For certain selected specific indications, the recommended duration or dosage and duration of doxycycline hyclate delayed-release tablets (MPC) in adult patients are as follows:
  1. Streptococcal infections, therapy should be continued for 10 days.
  2. Uncomplicated urethral, endocervical, or rectal infection caused by C. trachomatis: 100 mg, by mouth, twice-a-day for 7 days.
  3. Uncomplicated gonococcal infections in adults (except anorectal infections in men): 100 mg, by mouth, twice-a-day for 7 days. As an alternate single visit dose, administer 300 mg followed in one hour by a second 300 mg dose.
  4. Nongonococcal urethritis (NGU) caused by U. urealyticum: 100 mg, by mouth, twice-a-day for 7 days.
  5. Syphilis – early: Patients who are allergic to penicillin should be treated with doxycycline 120 mg, by mouth, twice-a-day for 2 weeks.
  6. Syphilis of more than one year's duration: Patients who are allergic to penicillin should be treated with doxycycline 100 mg, by mouth, twice-a-day for 4 weeks.
  7. Acute epididymo-orchitis caused by N. gonorrhoeae: 100 mg, by mouth, twice-a-day for at least 10 days.
  8. Acute epididymo-orchitis caused by C. trachomatis: 100 mg, by mouth, twice-a-day for at least 10 days

2.4 Dosage in Pediatric Patients

- For all pediatric patients weighing less than 45 kg with severe or life threatening infections (e.g., anthrax, Rocky Mountain spotted fever), the recommended dosage of doxycycline is 2.2 mg per kg of body weight administered every 12 hours. Pediatric patients weighing 45 kg or more should receive the adult dose [see Warnings and Precautions (5.1)].
- For pediatric patients with less severe disease (greater than 8 years of age and weighing less than 45 kg), the recommended dosage schedule of doxycycline is 4.4 mg per kg of body weight divided into two doses on the first day of treatment, followed by a maintenance dose of 2.2 mg per kg of body weight (given as a single daily dose or divided into twice daily doses). For pediatric patients weighing over 45 kg, the usual adult dose should be used.

2.5 Dosage for Prophylaxis of Malaria

For adults, the recommended dose of doxycycline hyclate delayed-release tablets is 100 mg daily. For pediatric patients 8 years of age and older, the recommended dose is 2 mg/kg administered once daily up to the adult dose. Pediatric patients weighing 45 kg or more should receive the adult dose.

Prophylaxis should begin 1 or 2 days before travel to the malarious area. Prophylaxis should be continued daily during travel in the malarious area and for 4 weeks after the traveler leaves the malarious area.

2.6 Dosage for Inhalational Anthrax (Post-Exposure)

For adults the recommended dosage is 100 mg of doxycycline hyclate delayed-release tablets, by mouth, twice-a-day for 60 days.

For pediatric patients weighing less than 45 kg, the recommended dosage of doxycycline hyclate delayed-release tablets is 2.2 mg/kg of body weight, by mouth, twice-a-day for 60 days. Pediatric patients weighing 45 kg or more should receive the adult dose.

2.7 Sprinkling the Tablet Over Applesauce

Doxycycline hyclate delayed-release tablets may also be administered by carefully breaking up the tablet and sprinkling the tablet contents (delayed-release pellets) on a spoonful of applesauce. The delayed-release pellets must not be crushed or damaged when breaking up the tablet. Any loss of pellets in the transfer would prevent using the dose. The applesauce/doxycycline hyclate delayed-release tablets mixture should be swallowed immediately without chewing and may be followed by a glass of water if desired. The applesauce should not be hot, and it should be soft enough to be swallowed without chewing. In the event that a prepared dose of applesauce/doxycycline hyclate delayed-release tablets mixture cannot be taken immediately, the mixture should be discarded and not stored for later use.

3 DOSAGE FORMS AND STRENGTHS

Doxycycline hyclate delayed-release tablets, USP 80 mg are white, oval scored tablets containing yellow pellets and debossed with "D|8" on one face and plain on the other. Each tablet contains specially coated pellets of doxycycline hyclate equivalent to 80 mg of doxycycline.

Doxycycline hyclate delayed-release tablets, 200 mg are white, oval scored tablets containing yellow pellets and debossed with "D|D" on one face and plain on the other. Each tablet contains specially coated pellets of doxycycline hyclate equivalent to 200 mg of doxycycline.

4 CONTRAINDICATIONS

Doxycycline hyclate delayed-release tablets are contraindicated in persons who have shown hypersensitivity to any of the tetracyclines.

5 WARNINGS AND PRECAUTIONS

5.1 Tooth Development

The use of drugs of the tetracycline-class during tooth development (last half of pregnancy, infancy and childhood to the age of 8 years) may cause permanent discoloration of the teeth (yellow-gray-brown). This adverse reaction is more common during long-term use of the drugs but it has been observed following repeated short-term courses. Enamel hypoplasia has also been reported. Use doxycycline hyclate delayed-release tablets in pediatric patients 8 years of age or less only when the potential benefits are expected to outweigh the risks in severe or life-threatening conditions (e.g., anthrax, Rocky Mountain spotted fever), particularly when there are no alternative therapies.

5.2 Clostridioides difficile-Associated Diarrhea

Clostridioides difficile associated diarrhea (CDAD) has been reported with use of nearly all antibacterial agents, including doxycycline hyclate delayed-release tablets, and may range in severity from mild diarrhea to fatal colitis. Treatment with antibacterial agents alters the normal flora of the colon leading to overgrowth of C. difficile.

C. difficile produces toxins A and B which contribute to the development of CDAD. Hypertoxin producing strains of C. difficile cause increased morbidity and mortality, as these infections can be refractory to antimicrobial therapy and may require colectomy. CDAD must be considered in all patients who present with diarrhea following antibacterial use. Careful medical history is necessary since CDAD has been reported to occur over two months after the administration of antibacterial agents.

If CDAD is suspected or confirmed, ongoing antibacterial use not directed against C. difficile may need to be discontinued. Appropriate fluid and electrolyte management, protein supplementation, antibacterial treatment of C. difficile, and surgical evaluation should be instituted as clinically indicated.

5.3 Photosensitivity

Photosensitivity manifested by an exaggerated sunburn reaction has been observed in some individuals taking tetracyclines. Patients apt to be exposed to direct sunlight or ultraviolet light should be advised that this reaction can occur with tetracycline drugs, and treatment should be discontinued at the first evidence of skin erythema.

5.4 Potential for Microbial Overgrowth

Doxycycline hyclate delayed-release tablets may result in overgrowth of non-susceptible organisms, including fungi. If superinfection occurs, the antibacterial should be discontinued and appropriate therapy instituted.

5.5 Severe Skin Reactions

Severe skin reactions, such as exfoliative dermatitis, erythema multiforme, Stevens-Johnson syndrome, toxic epidermal necrolysis, and drug reaction with eosinophilia and systemic symptoms (DRESS) have been reported in patients receiving doxycycline. Fixed drug eruptions have occurred with doxycycline and have been associated with worsening severity upon subsequent administrations, including generalized bullous fixed drug eruption [see Adverse Reactions (6)]. If severe skin reactions occur, discontinue doxycycline hyclate delayed-release tablets immediately and institute appropriate therapy.

5.6 Intracranial Hypertension

Intracranial hypertension (IH, pseudotumor cerebri) has been associated with the use of tetracycline including doxycycline hyclate delayed-release tablets. Clinical manifestations of IH include headache, blurred vision, diplopia, and vision loss; papilledema can be found on fundoscopy. Women of childbearing age who are overweight or have a history of IH are at greater risk for developing tetracycline associated IH. Avoid concomitant use of isotretinoin and doxycycline hyclate delayed-release tablets because isotretinoin is also known to cause pseudotumor cerebri.

Although IH typically resolves after discontinuation of treatment, the possibility for permanent visual loss exists. If visual disturbance occurs during treatment, prompt ophthalmologic evaluation is warranted. Since intracranial pressure can remain elevated for weeks after drug cessation patients should be monitored until they stabilize.

5.7 Skeletal Development

All tetracyclines form a stable calcium complex in any bone-forming tissue. A decrease in fibula growth rate has been observed in prematures given oral tetracycline in doses of 25 mg/kg every six hours. This reaction was shown to be reversible when the drug was discontinued.

Results of animal studies indicate that tetracyclines cross the placenta, are found in fetal tissues, and can have toxic effects on the developing fetus (often related to retardation of skeletal development). Evidence of embryotoxicity also has been noted in animals treated early in pregnancy. If any tetracycline is used during pregnancy or if the patient becomes pregnant while taking these drugs, the patient should be apprised of the potential hazard to the fetus.

5.8 Antianabolic Action

The antianabolic action of the tetracyclines may cause an increase in BUN. Studies to date indicate that this does not occur with the use of doxycycline in patients with impaired renal function.

5.9 Malaria

Doxycycline offers substantial but not complete suppression of the asexual blood stages of Plasmodium strains.

Doxycycline does not suppress P. falciparum's sexual blood stage gametocytes. Subjects completing this prophylactic regimen may still transmit the infection to mosquitoes outside endemic areas.

5.10 Development of Drug-Resistant Bacteria

Prescribing doxycycline hyclate delayed-release tablets in the absence of a proven or strongly suspected bacterial infection or a prophylactic indication is unlikely to provide benefit to the patient and increases the risk of the development of drug-resistant bacteria.

5.11 Laboratory Monitoring for Long-Term Therapy

In long-term therapy, periodic laboratory evaluation of organ systems, including hematopoietic, renal, and hepatic studies should be performed.

6 ADVERSE REACTIONS

6.1 Clinical Trial Experience

The safety and efficacy of doxycycline hyclate delayed-release tablets, 200 mg as a single daily dose was evaluated in a multicenter, randomized, double-blind, active-controlled study. Doxycycline hyclate delayed-release tablets, 200 mg was given orally once-a-day for 7 days and compared to doxycycline hyclate capsules 100 mg given orally twice daily for 7 days for the treatment of men and women with uncomplicated urogenital C. trachomatis infection.

Adverse reactions in the Safety Population were reported by 99 (40.2%) subjects in the doxycycline hyclate delayed-release tablets, 200 mg treatment group and 132 (53.2%) subjects in the doxycycline hyclate capsules reference treatment group. Most adverse reactions were mild in intensity. The most commonly reported adverse reactions in both treatment groups were nausea, vomiting, diarrhea, and bacterial vaginitis, Table 1.

Table 1: Adverse Reactions Reported in Greater than or Equal to 2% of Subjects
Adverse Reactions | Doxycycline hyclate delayed-release tablets Tablets, 200 mg N = 246
 | n (%)
Subjects with any AE | 99 (40.2)
Nausea | 33 (13.4)
Vomiting | 20 (8.1)
Headache | 5 (2.0)
Diarrhea | 8 (3.3)
Abdominal Pain Upper | 5 (2.0)
Vaginitis Bacterial | 8 (3.3)
Vulvovaginal Mycotic Infection | 5 (2.0)

Because clinical trials are conducted under prescribed conditions, adverse reaction rates observed in the clinical trial may not always reflect the rates observed in practice.

6.2 Postmarketing Experience

The following adverse reactions have been identified during post-approval use of doxycycline. Because these reactions are reported voluntarily from a population of uncertain size, it is not always possible to reliably estimate a causal relationship to drug exposure.

Due to oral doxycycline's virtually complete absorption, side effects to the lower bowel, particularly diarrhea, have been infrequent. The following adverse reactions have been observed in patients receiving tetracyclines:

Gastrointestinal: Anorexia, nausea, vomiting, diarrhea, glossitis, dysphagia, enterocolitis, inflammatory lesions (with monilial overgrowth) in the anogenital region and pancreatitis. Hepatotoxicity has been reported. These reactions have been caused by both the oral and parenteral administration of tetracyclines. Superficial discoloration of the adult permanent dentition, reversible upon drug discontinuation and professional dental cleaning has been reported. Permanent tooth discoloration and enamel hypoplasia may occur with drugs of the tetracycline class when used during tooth development [see Warnings and Precautions (5.1)]. Esophagitis and esophageal ulcerations have been reported in patients receiving capsule and tablet forms of drugs in the tetracycline- class. Most of these patients took medications immediately before going to bed [see Dosage and Administration (2.1)].

Skin: Maculopapular and erythematous rashes, Stevens-Johnson syndrome, toxic epidermal necrolysis, exfoliative dermatitis, erythema multiforme, and fixed drug eruption have been reported. Photosensitivity is discussed above [see Warnings and Precautions (5.3)].

Renal: Rise in BUN has been reported and is apparently dose-related [see Warnings and Precautions (5.8)].

Hypersensitivity reactions: Urticaria, angioneurotic edema, anaphylaxis, anaphylactoid purpura, serum sickness, pericarditis, and exacerbation of systemic lupus erythematosus, and drug reaction with eosinophilia and systemic symptoms (DRESS).

Blood: Hemolytic anemia, thrombocytopenia, neutropenia, and eosinophilia have been reported.

Intracranial Hypertension: Intracranial hypertension (IH, pseudotumor cerebri) has been associated with the use of tetracycline [see Warnings and Precautions (5.6)]

Thyroid Gland Changes: When given over prolonged periods, tetracyclines have been reported to produce brown-black microscopic discoloration of thyroid glands. No abnormalities of thyroid function are known to occur.

Psychiatric: Depression, anxiety, suicidal ideation, insomnia, abnormal dreams, hallucination

7 DRUG INTERACTIONS

7.1 Anticoagulant Drugs

Because tetracyclines have been shown to depress plasma prothrombin activity, patients who are on anticoagulant therapy may require downward adjustment of their anticoagulant dosage.

7.2 Penicillin

Since bacteriostatic drugs may interfere with the bactericidal action of penicillin, it is advisable to avoid giving tetracyclines in conjunction with penicillin.

7.3 Antacids and Iron Preparations

Absorption of tetracyclines is impaired by antacids containing aluminum, calcium, or magnesium, bismuth subsalicylate, and iron-containing preparations.

7.4 Oral Contraceptives

Concurrent use of tetracycline may render oral contraceptives less effective.

7.5 Barbiturates and Anti-Epileptics

Barbiturates, carbamazepine, and phenytoin decrease the half-life of doxycycline.

7.6 Drug/Laboratory Test Interactions

False elevations of urinary catecholamines may occur due to interference with the fluorescence test.

8 USE IN SPECIFIC POPULATIONS

8.1 Pregnancy

Risk Summary

There are no adequate and well-controlled studies on the use of doxycycline in pregnant women. The vast majority of reported experience with doxycycline during human pregnancy is short-term, first trimester exposure. There are no human data available to assess the effects of long-term therapy of doxycycline in pregnant women such as that proposed for the treatment of anthrax exposure. An expert review of published data on experiences with doxycycline use during pregnancy by TERIS - the Teratogen Information System - concluded that therapeutic doses during pregnancy are unlikely to pose a substantial teratogenic risk (the quantity and quality of data were assessed as limited to fair), but the data are insufficient to state that there is no risk (see Data).^1

In the US general population the estimated background risk of major birth defects and miscarriage in clinically recognized pregnancies is 2-4% and 15-20%, respectively.

Clinical Considerations

Embryo/Fetal Risk

Results of animal studies indicate that tetracyclines cross the placenta, are found in fetal tissues, and can have toxic effects on the developing fetus (often related to retardation of skeletal development). Evidence of embryotoxicity also has been noted in animals treated early in pregnancy. If any tetracycline is used during pregnancy or if the patient becomes pregnant while taking these drugs, the patient should be apprised of the potential hazard to the fetus [see Warnings and Precautions (5.1, 5.6)].

Data

Human Data

A case-control study (18,515 mothers of infants with congenital anomalies and 32,804 mothers of infants with no congenital anomalies) shows a weak but marginally statistically significant association with total malformations and use of doxycycline anytime during pregnancy. Sixty-three (0.19%) of the controls and 56 (0.30%) of the cases were treated with doxycycline. This association was not seen when the analysis was confined to maternal treatment during the period of organogenesis (that is, in the second and third months of gestation), with the exception of a marginal relationship with neural tube defect based on only two-exposed cases.^2

A small prospective study of 81 pregnancies describes 43 pregnant women treated for 10 days with doxycycline during early first trimester. All mothers reported their exposed infants were normal at 1 year of age.^3

8.2 Lactation

Risk Summary

Tetracyclines are excreted in human milk, however, the extent of absorption of tetracyclines including doxycycline, by the breastfed infant is not known. Short-term use by lactating women is not necessarily contraindicated. The effects of prolonged exposure to doxycycline in breast milk production and breast fed neonates, infants and children are unknown^4. The developmental and health benefits of breastfeeding should be considered along with the mother's clinical need for doxycycline hyclate delayed-release tablets and any potential adverse effects on the breast fed child from doxycycline hyclate delayed-release tablets or from the underlying maternal condition [see Warnings and Precautions (5.1, 5.6)].

8.4 Pediatric use

Because of the effects of drugs of the tetracycline-class on tooth development and growth, use doxycycline hyclate delayed-release tablets in pediatric patients 8 years of age or less only when the potential benefits are expected to outweigh the risks in severe or life-threatening conditions (e.g., anthrax, Rocky Mountain spotted fever), particularly, when there are no alternative therapies [see Dosage and Administration (2.1, 2.3) and Warnings and Precautions (5.1, 5.6)].

8.5 Geriatric use

Clinical studies of doxycycline hyclate delayed-release tablets did not include sufficient numbers of subjects aged 65 and over to determine whether they respond differently from younger subjects. Other reported clinical experience has not identified differences in responses between the elderly and younger patients.

Doxycycline hyclate delayed-release tablets, USP, 50 mg contain 3 mg (0.131 mEq) of sodium.

Doxycycline hyclate delayed-release tablets, USP, 75 mg contain 4.5 mg (0.196 mEq) of sodium.

Doxycycline hyclate delayed-release tablets, USP, 80 mg contain 4.8 mg (0.209 mEq) of sodium.

Doxycycline hyclate delayed-release tablets, USP, 100 mg contain 6 mg (0.261 mEq) of sodium.

Doxycycline hyclate delayed-release tablets, USP, 150 mg contain 9 mg (0.392 mEq) of sodium.

Doxycycline hyclate delayed-release tablets, USP, 200 mg contain 12 mg (0.522 mEq) of sodium.

10 OVERDOSAGE

In case of overdosage, discontinue medication, treat symptomatically and institute supportive measures. Dialysis does not alter serum half-life and thus would not be of benefit in treating cases of overdosage.

11 DESCRIPTION

Doxycycline hyclate delayed-release tablets, contain specially coated pellets of doxycycline hyclate, a tetracycline class drug synthetically derived from oxytetracycline, in a delayed-release formulation for oral administration.

The structural formula for doxycycline hyclate is:

with a molecular formula of C22H24N2O8, HCl, ½ C2H6O, ½ H2O and a molecular weight of 512.9. The chemical name for doxycycline hyclate is [4S(4aR,5S,5aR,6R,12aS)]-4-(dimethylamino)-1,4,4a,5,5a,6,11,12a-octahydro-3,5,10,12,12a-pentahydroxy-6- methyl-1,11-deoxonaphthacene-2-carboxamide monohydrochloride, compound with ethyl alcohol (2:1), monohydrate. Doxycycline hyclate is a yellow crystalline powder soluble in water and in solutions of alkali hydroxides and carbonates. Doxycycline has a high degree of lipid solubility and a low affinity for calcium binding. It is highly stable in normal human serum. Doxycycline will not degrade into an epianhydro form.

Each tablet contains doxycycline 50 mg, 75 mg, 80 mg, 100 mg, 150 mg or 200 mg (equivalent to doxycycline hyclate 57.7 mg, 86.6 mg, 92.3 mg, 115.4 mg, 173.1 mg or 230.8 mg). Inactive ingredients in the tablet formulation are: lactose monohydrate; microcrystalline cellulose; sodium lauryl sulfate; sodium chloride; talc; anhydrous lactose; corn starch; crospovidone; magnesium stearate; cellulosic polymer coating.

Each doxycycline hyclate delayed-release tablets 50 mg tablet contains 3 mg (0.131 mEq) of sodium, each doxycycline hyclate delayed-release tablets 75 mg tablet contains 4.5 mg (0.196 mEq) of sodium, each doxycycline hyclate delayed-release tablets 80 mg tablet contains 4.8 mg (0.209 mEq) of sodium, each doxycycline hyclate delayed-release tablets 100 mg tablet contains 6 mg (0.261 mEq) of sodium, each doxycycline hyclate delayed-release tablets 150 mg tablet contains 9 mg (0.392 mEq) of sodium, and each doxycycline hyclate delayed-release tablets 200 mg tablet contains 12 mg (0.522 mEq) of sodium.

12 CLINICAL PHARMACOLOGY

12.1 Mechanism of Action

Doxycycline is a tetracycline-class antimicrobial drug [see Microbiology (12.4)].

12.3 Pharmacokinetics

Following single and multiple-dose administration of doxycycline hyclate delayed-release tablets, 200 mg to adult volunteers, average peak plasma doxycycline concentration (Cmax) was 4.6 mcg/mL and 6.3 mcg/mL, respectively with median tmax of 3 hours; the corresponding mean plasma concentration values 24 hours after single and multiple doses were 1.5 mcg/mL and 2.3 mcg/mL, respectively.

Absorption

Doxycycline is virtually completely absorbed after oral administration.

Effect of Food

The mean Cmax and AUC 0-∞ of doxycycline are 24% and 13% lower, respectively, following single dose administration of doxycycline hyclate delayed-release tablets, 100 mg with a high fat meal (including milk) compared to fasted conditions. The mean Cmax of doxycycline is 19% lower and the AUC 0-∞ is unchanged following single dose administration of doxycycline hyclate delayed-release tablets, 150 mg with a high fat meal (including milk) compared to fasted conditions. The clinical significance of these decreases is unknown. Doxycycline bioavailability from doxycycline hyclate delayed-release tablets, 200 mg was not affected by food, but the incidence of nausea was higher in fasted subjects. The 200 mg tablets may be administered without regard to meals.

When doxycycline hyclate delayed-release tablets are sprinkled over applesauce and taken with or without water, the extent of doxycycline absorption is unchanged, but the rate of absorption is increased slightly.

Elimination

Tetracyclines are concentrated in bile by the liver and excreted in the urine and feces at high concentrations and in a biologically active form. Excretion of doxycycline by the kidney is about 40%/72 hours in individuals with a creatinine clearance of about 75 mL/min. This percentage may fall as low as 1-5%/72 hours in individuals with a creatinine clearance below 10 mL/min.

Specific Populations

Patients with Renal Impairment

Studies have shown no significant difference in the serum half-life of doxycycline (range 18 to 22 hours) in individuals with normal and severely impaired renal function. Hemodialysis does not alter the serum half-life.

Pediatric Patients

Population pharmacokinetic analysis of sparse concentration-time data of doxycycline. Following standard of care intravenous and oral dosing in 44 children (2-18 years of age) showed that allometrically-scaled clearance of doxycycline in children ≥2 to ≤8 years of age (median [range] 3.58 [2.27-10.82] L/h/70 kg, N=11) did not differ significantly from children >8 to 18 years of age (3.27 [1.11-8.12] L/h/70 kg, N=33). For pediatric patients weighing ≤45 kg, body weight normalized doxycycline CL in those ≥2 to ≤8 years of age (median [range] 0.071 [0.041-0.202] L/kg/h, N=l0) did not differ significantly from those >8 to 18 years of age (0.081 [0.035-0.126] L/kg/h, N=8). In pediatric patients weighing >45 kg no clinically significant differences in body weight normalized doxycycline CL were observed between those ≥2 to ≤8 years (0.050 L/kg/h, N=l) and those >8 years of age (0.044 [0.014-0.121] L/kg/h, N=25). No clinically significant difference in CL differences between oral and IV were observed in the small cohort of pediatric patients who received the oral (N=l9) or IV (N=21) formulation alone.

12.4 Microbiology

Mechanism of Action

Doxycycline inhibits bacterial protein synthesis by binding to the 30S ribosomal subunit. Doxycycline has bacteriostatic activity against a broad range of Gram-positive and Gram-negative bacteria.

Resistance

Cross-resistance between tetracyclines is common.

Antimicrobial Activity

Doxycycline has been shown to be active against most isolates of the following microorganisms, both in vitro and in clinical infections. [see Indications and Usage (1)].

Gram-Negative Bacteria

Acinetobacter species
Bartonella bacilliformis
Brucella species
Campylobacter fetus
Enterobacter aerogenes
Escherichia coli
Francisella tularensis
Haemophilus ducreyi
Haemophilus influenzae
Klebsiella granulomatis
Klebsiella species
Neisseria gonorrhoeae
Shigella species
Vibrio cholerae
Yersinia pestis

Gram-Positive Bacteria

Bacillus anthracis
Listeria monocytogenes
Streptococcus pneumoniae

Anaerobic Bacteria

Clostridium species
Fusobacterium fusiforme
Propionibacterium acnes

Other Bacteria

Norcardiae and other aerobic Actinomyces species
Borrelia recurrentis
Chlamydophila psittaci
Chlamydia trachomatis
Mycoplasma pneumoniae
Rickettsiae
Treponema pallidum
Treponema pallidum subspecies pertenue
Ureaplasma urealyticum

Parasites

Balantidium coli
Entamoeba species
Plasmodium falciparum [Doxycycline has been found to be active against the asexual erythrocytic forms of Plasmodium falciparum but not against the gametocytes of P. falciparum. The precise mechanism of action of the drug is not known.]

Susceptibility Testing

For specific information regarding susceptibility test interpretive criteria and associated test methods and quality control standards recognized by FDA for this drug, please see: https://www.fda.gov/STIC.

13 NONCLINICAL TOXICOLOGY

13.1 Carcinogenesis, Mutagenesis, Impairment of Fertility

Long-term studies in animals to evaluate carcinogenic potential of doxycycline have not been conducted. However, there has been evidence of oncogenic activity in rats in studies with the related antibacterials, oxytetracycline (adrenal and pituitary tumors) and minocycline (thyroid tumors). Likewise, although mutagenicity studies of doxycycline have not been conducted, positive results in in vitro mammalian cell assays have been reported for related antibacterials (tetracycline, oxytetracycline).

Doxycycline administered orally at dosage levels as high as 250 mg/kg/day had no apparent effect on the fertility of female rats. Effect on male fertility has not been studied.

13.2 Animal Toxicology and/or Pharmacology

Hyperpigmentation of the thyroid has been produced by members of the tetracycline- class in the following species: in rats by oxytetracycline, doxycycline, tetracycline PO4, and methacycline; in minipigs by doxycycline, minocycline, tetracycline PO4, and methacycline; in dogs by doxycycline and minocycline; in monkeys by minocycline.

Minocycline, tetracycline PO4, methacycline, doxycycline, tetracycline base, oxytetracycline HCl, and tetracycline HCl, were goitrogenic in rats fed a low iodine diet. This goitrogenic effect was accompanied by high radioactive iodine uptake. Administration of minocycline also produced a large goiter with high radioiodine uptake in rats fed a relatively high iodine diet.

Treatment of various animal species with this class of drugs has also resulted in the induction of thyroid hyperplasia in the following: in rats and dogs (minocycline); in chickens (chlortetracycline); and in rats and mice (oxytetracycline). Adrenal gland hyperplasia has been observed in goats and rats treated with oxytetracycline.

Results of animal studies indicate that tetracyclines cross the placenta and are found in fetal tissues.

14 CLINICAL STUDIES

This was a randomized, double-blind, active-controlled, multicenter trial which enrolled 495 subjects, between 19 to 45 years of age with a confirmed diagnosis of urogenital C. trachomatis infection less than 14 days prior to enrollment, or partner(s) of a subject with a known positive test for urogenital C. trachomatis infection.

The primary purpose of this study was to evaluate the efficacy and safety of doxycycline hyclate delayed-release tablets Tablets, 200 mg once daily versus doxycycline hyclate capsules, 100 mg twice daily for seven days for the treatment of uncomplicated urogenital C. trachomatis infection. The primary efficacy objective was to demonstrate non-inferiority of the doxycycline hyclate delayed-release tablets, 200 mg once daily treatment regimen versus the doxycycline 100 mg twice daily treatment regimen for the indication using a negative nucleic acid amplification test (NAAT) at the test of cure visit (day 28) in the mITT population (subjects who were positive at baseline and took at least one day of study drug).

Table 2: Primary Efficacy Outcome – Microbiological Cure of C. trachomatis at Day 28
mITT Population |  | Doxycycline hyclate delayed-release tablets, 200 mg once daily Cure Rate (%) | Doxycycline hyclate capsules, 100 mg twice daily Cure Rate (%) | Difference (%)
 | N | 188 | 190
 | Microbiological Cure, n (%) | 163 (86.7) | 171 (90.0) | -3.3%
 | 95% Confidence Interval for Cure Rate |  |  | -10.3, 3.7

15 REFERENCES

1. Friedman JM, Polifka JE. Teratogenic Effects of Drugs. A Resource for Clinicians (TERIS). Baltimore, MD: The Johns Hopkins University Press: 2000: 149-195.
2. Cziezel AE and Rockenbauer M. Teratogenic study of doxycycline. Obstet Gynecol 1997; 89: 524-528.
3. Horne HW Jr. and Kundsin RB. The role of mycoplasma among 81 consecutive pregnancies: a prospective study. Int J Fertil 1980; 25: 315-317.
4. Drugs and Lactation Database (LactMed) [Internet]. Bethesda (MD): National Library of Medicine (US); [Last Revision Date 2015 March 10; cited 2016 Jan]. Doxycycline; LactMed Record Number: 100; [about 3 screens]. Available from: http://toxnet.nlm.nih.gov/newtoxnet/lactmed.htm .

16 HOW SUPPLIED/STORAGE AND HANDLING

Doxycycline hyclate delayed-release tablets, USP, 80 mg are white, oval scored tablets containing yellow pellets and debossed with "D|8" on one face and plain on the other. Each tablet contains specially coated pellets of doxycycline hyclate equivalent to 80 mg of doxycycline.

Bottles of 30 tablets
NDC 51862-571-30

Doxycycline hyclate delayed-release tablets, 200 mg are white, oval scored tablets containing yellow pellets and debossed with "D|D" on one face and plain on the other. Each tablet contains specially coated pellets of doxycycline hyclate equivalent to 200 mg of doxycycline.

Bottles of 30 tablets | Bottles of 60 tablets
NDC 68308-716-30 | NDC 68308-716-60

STORAGE AND HANDLING

Store at 25°C (77°F); excursions permitted to 15 – 30°C (59 – 86°F) [see USP Controlled Room Temperature]. Dispense in a tight, light-resistant container (USP).

17 PATIENT COUNSELING INFORMATION

Advise patients taking doxycycline for malaria prophylaxis:

- that no present-day antimalarial agent, including doxycycline, guarantees protection against malaria.
- to avoid being bitten by mosquitoes by using personal protective measures that help avoid contact with mosquitoes, especially from dusk to dawn (for example, staying in well-screened areas, using mosquito nets, covering the body with clothing, and using an effective insect repellent).
- that doxycycline prophylaxis:
  - should begin 1 to 2 days before travel to the malarious area,
  - should be continued daily while in the malarious area and after leaving the malarious area,
  - should be continued for 4 further weeks to avoid development of malaria after returning from an endemic area,
  - should not exceed 4 months.

Advise all patients taking doxycycline:

- to avoid excessive sunlight or artificial ultraviolet light while receiving doxycycline and to discontinue therapy if phototoxicity (for example, skin eruptions, etc.) occurs. Sunscreen or sunblock should be considered [see Warnings and Precautions (5.3)].
- to drink fluids liberally along with doxycycline to reduce the risk of esophageal irritation and ulceration [see Adverse Reactions (6.1)].
- that the absorption of tetracyclines is reduced when taken with foods, especially those that contain calcium. However, the absorption of doxycycline is not markedly influenced by simultaneous ingestion of food or milk [see Drug Interactions (7.3)].
- that the absorption of tetracyclines is reduced when taken with antacids containing aluminum, calcium or magnesium, bismuth subsalicylate, and iron-containing preparations [see Drug Interactions (7.3)].
- that the use of doxycycline might increase the incidence of vaginal candidiasis.

Advise patients that diarrhea is a common problem caused by antibacterials which usually ends when the antibacterial is discontinued. Sometimes after starting treatment with antibacterials, patients can develop watery and bloody stools (with or without stomach cramps and fever) even as late as two or more months after having taken the last dose of antibacterial. If this occurs, patients should contact their physician as soon as possible.

Patients should be counseled that antibacterial drugs including doxycycline hyclate delayed-release tablets should only be used to treat bacterial infections. They do not treat viral infections (e.g., the common cold). When doxycycline hyclate delayed-release tablets is prescribed to treat a bacterial infection, patients should be told that although it is common to feel better early in the course of therapy, the medication should be taken exactly as directed. Skipping doses or not completing the full course of therapy may (1) decrease the effectiveness of the immediate treatment and (2) increase the likelihood that bacteria will develop resistance and will not be treatable by Doxycycline hyclate delayed-release tablets or other antibacterial drugs in the future.

17.1 Instructions for Breaking the 150 mg Doxycycline Hyclate Delayed-Release Dual-Scored Tablet

The tablet is marked with separation lines (score lines) and may be broken at these score lines to provide any of the following doses.

- 150 mg treatment (the entire tablet is taken)

- 100 mg treatment (two thirds of the tablet or two 50 mg tablet segments are taken)

- 50 mg treatment (one third of the tablet is taken)

To break the tablet, the tablet is held between the thumbs and index fingers close to the appropriate score line. Then, with the score line facing the patient, enough pressure is applied to snap the tablet segments apart (segments that do not break along the score line should not be used).

FDA-Approved Patient Labeling Doxycycline hyclate delayed-release tablets, 50 mg, 75 mg, 80 mg, 100 mg, 150 mg and 200 mg Instructions for Breaking the 150 mg Doxycycline hyclate delayed-release dual-scored tablet

Your doctor may find it necessary to adjust your dosage of doxycycline hyclate delayed-release tablets to obtain the proper treatment response. The tablet is marked with separation lines (score lines) and may be broken at these score lines to provide any of the following doses. If your doctor prescribed:

- 150 mg treatment (take the entire tablet)

- 100 mg treatment (take two thirds of the tablet or two 50 mg tablet segments)

- 50 mg treatment (take one third of the tablet)

To break the tablet, hold the tablet between your thumbs and index fingers close to the appropriate score line. Then, with the score line facing you, apply enough pressure to snap the tablet segments apart (do not use segments that do not break along the score line).

Distributed by:
Mayne Pharma
Raleigh, NC 27609

61449

PRINCIPAL DISPLAY PANEL - 75 mg Tablet Bottle Label

NDC 68308-775-60

Doxycycline Hyclate
Delayed-Release
Tablets, USP

Do not chew or crush tablets.

Each tablet contains specially coated pellets
of doxycycline hyclate equivalent to 75 mg of
doxycycline.

75 mg

Rx Only

mayne pharma

60 Tablets

PRINCIPAL DISPLAY PANEL - 100 mg Tablet Bottle Label

NDC 68308-710-10

Doxycycline Hyclate
Delayed-Release
Tablets, USP

Do not chew or crush tablets.

Each tablet contains specially coated pellets of
doxycycline hyclate equivalent to 100 mg of doxycycline.

100 mg

Rx Only

mayne pharma

100 Tablets

PRINCIPAL DISPLAY PANEL - 150 mg Tablet Bottle Label

NDC 68308-715-10

Doxycycline Hyclate
Delayed-Release
Tablets, USP

Do not chew or crush tablets.

Each tablet contains specially coated pellets of
doxycycline hyclate equivalent to 150 mg of doxycycline.

150 mg

Rx Only

mayne pharma

100 Tablets

PRINCIPAL DISPLAY PANEL - 200 mg Tablet Bottle Label

NDC 68308-716-30

Doxycycline Hyclate
Delayed-Release
Tablets, USP

Do not chew or crush tablets.

Each tablet contains specially coated pellets of
doxycycline hyclate equivalent to 200 mg of doxycycline.

200 mg

Rx Only

mayne pharma

30 Tablets